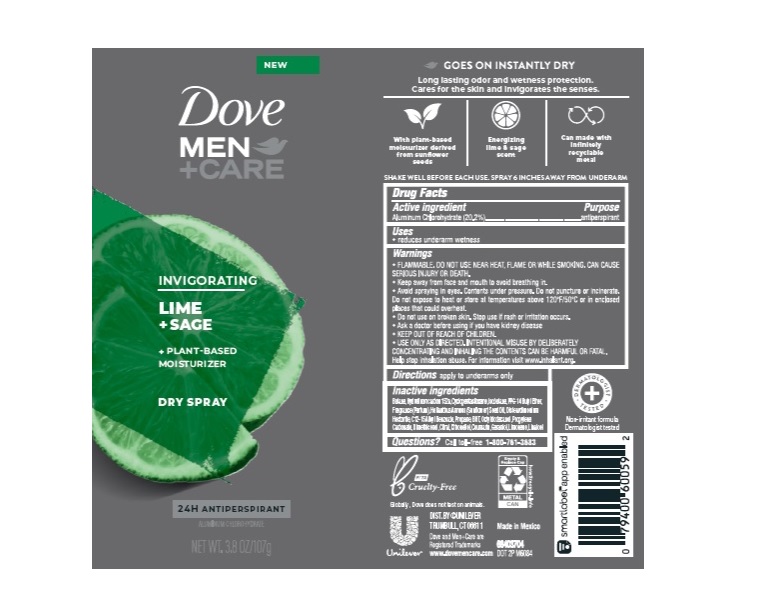 DRUG LABEL: Dove
NDC: 64942-1780 | Form: AEROSOL, SPRAY
Manufacturer: Conopco Inc. d/b/a/ Unilever
Category: otc | Type: HUMAN OTC DRUG LABEL
Date: 20241110

ACTIVE INGREDIENTS: ALUMINUM CHLOROHYDRATE 20.2 g/100 g
INACTIVE INGREDIENTS: BUTANE; 1,1-DIFLUOROETHANE; CYCLOMETHICONE 5; ISOBUTANE; PPG-14 BUTYL ETHER; SUNFLOWER OIL; ALKYL (C12-15) BENZOATE; PROPANE; PROPYLENE CARBONATE; DISTEARDIMONIUM HECTORITE; BUTYLATED HYDROXYTOLUENE; OCTYLDODECANOL; DIMETHICONOL (40 CST); CITRAL; .BETA.-CITRONELLOL, (R)-; COUMARIN; LIMONENE, (+)-; LINALOOL, (+/-)-; GERANIOL

Dove Men plus Care Dry Spray Lime + Sage 24H Antiperspirant

DOVE MEN PLUS CARE DRY SPRAY LIME + SAGE 24H ANTIPERSPIRANT - aluminum chlorohydrate aerosol, spray

Dove Men plus Care Dry Spray Lime + Sage 24H Antiperspirant

Drug Facts

Active ingredient
Aluminum Chlorohydrate (20.2%)

Purpose

antiperspirant

Uses

• reduces underarm wetness

Warnings

• FLAMMABLE. DO NOT USE NEAR HEAT, FLAME, OR WHILE SMOKING. CAN CAUSE SERIOUS INJURY OR DEATH
• Keep away from face and mouth to avoid breathing in.
• Avoid spraying in eyes. Contents under pressure. Do not puncture or incinerate. Do not expose to heat or store at temperatures above 120°F/50°C or in enclosed places that could overheat
• Do not use on broken skin. Stop use if rash or irritation occurs.
• Ask a doctor before using if you have kidney disease.
• USE ONLY AS DIRECTED. INTENTIONAL MISUSE BY DELIBERATELY CONCENTRATING AND INHALING THE CONTENTS CAN BE HARMFUL OR FATAL.
Help stop inhalation abuse. For information visit www.inhalant.org

• KEEP OUT OF REACH OF CHILDREN.

Directions

apply to underarms only

Inactive ingredients

Butane, Hydrofluorocarbon 152a, Cyclopentasiloxane, Isobutane, PPG-14 Butyl Ether, Fragrance (Parfum), Helianthus Annuus (Sunflower) Seed Oil, Disteardimonium Hectorite, C12-15 Alkyl Benzoate, Propane, BHT, Octyldodecanol, Propylene Carbonate, Dimethiconol, Citral, Citronellol, Coumarin, Geraniol, Limonene, Linalool

Questions?

Call toll-free 1-800-761-3683